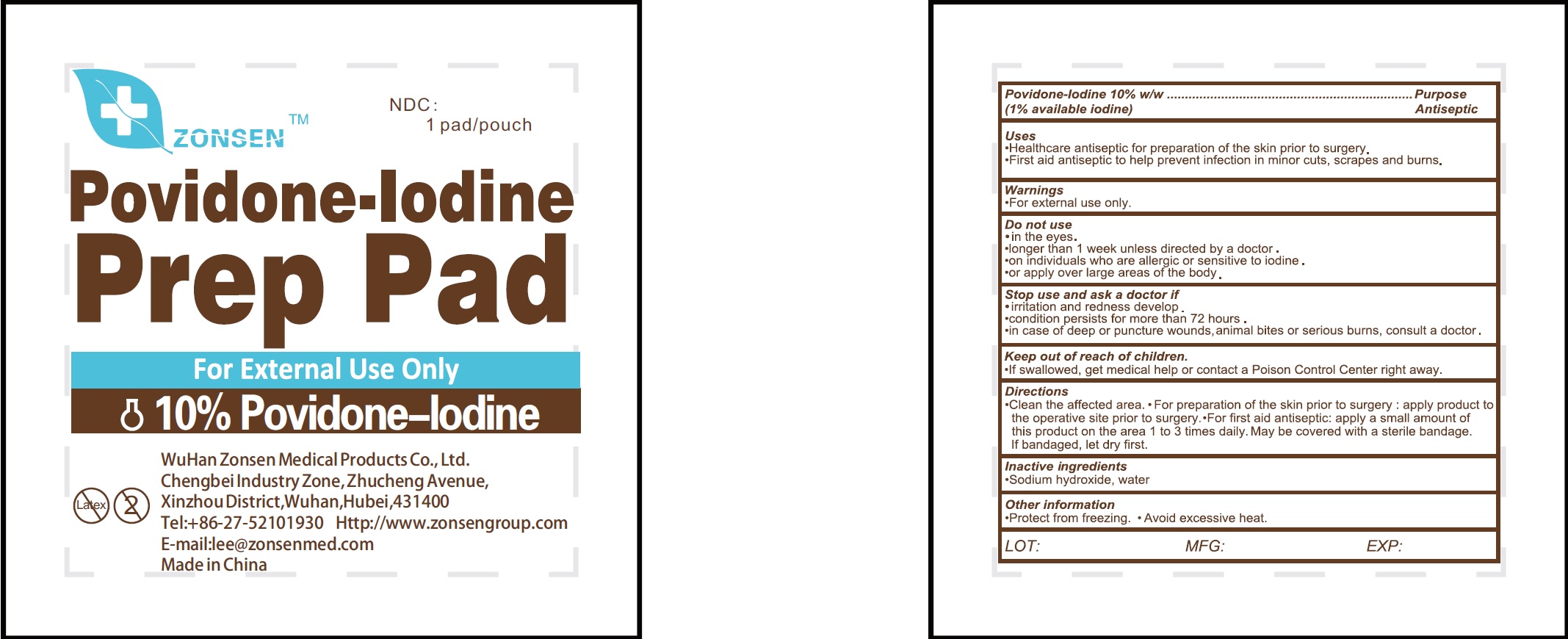 DRUG LABEL: Zonsen Povidone-Iodine Prep Pad
NDC: 72932-003 | Form: SWAB
Manufacturer: Wuhan Zonsen Medical Products Co., Ltd.
Category: otc | Type: HUMAN OTC DRUG LABEL
Date: 20190520

ACTIVE INGREDIENTS: POVIDONE-IODINE 100 mg/1 mL
INACTIVE INGREDIENTS: SODIUM HYDROXIDE; WATER

Zonsen Povidone-Iodine Prep Pad

Active Ingredients

Povidone-Iodine 10% w/w (1% available iodine)

Purpose

Antiseptic

Use

- Healthcare antiseptic for preparation of the skin prior to surgery.
- First aid antiseptic to help prevent infection in minor cuts, scrapes and burns.

Warnings

- For external use only.

Do not use

- in the eyes.
- longer than 1 week unless directed by a doctor.
- on individuals who are allergic or sensitive to iodine.
- or apply over large areas of the body.

Stop use and ask a doctor if

- If irritation and redness develop.
- condition persist for more than 72 hours.
- In case of deep or puncture wounds, animal bites or serious burns, consult a doctor.

Keep out of reach of children.

If swallowed, get medical help or contact a Poison Control Center right away.

Directions

- Clean the affected area.
- For preparation of the skin prior to surgery: apply product to the operative site prior to surgery
- For first aid antiseptic: apply a small amount of this product on the area 1 to 3 times daily. May be covered with a sterile bandage. If bandaged, let dry first.

Inactive Ingredients:

Sodium hydroxide, water

Other information

- Protect from freezing
- Avoid excessive heat.